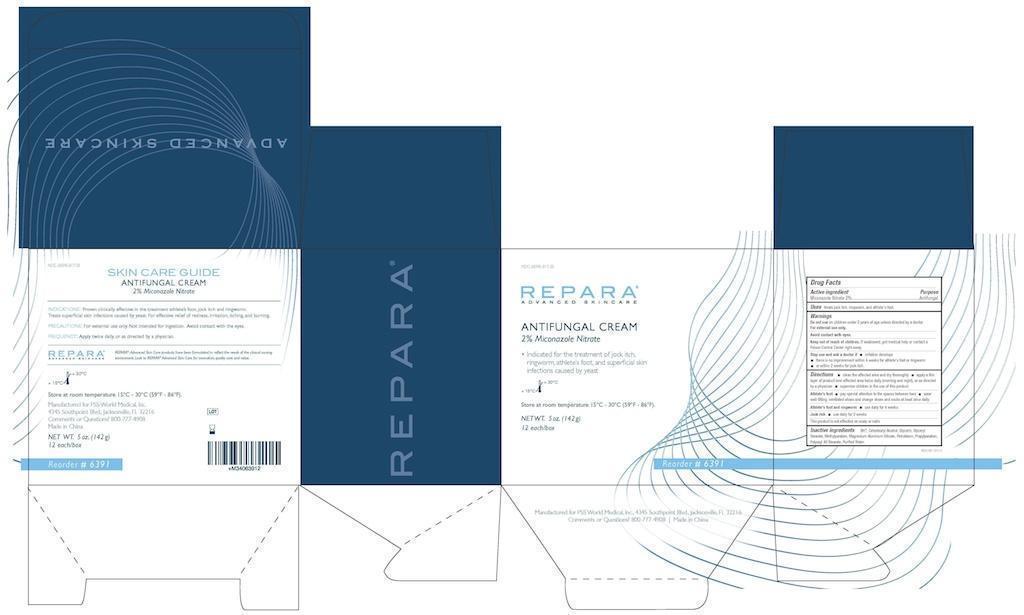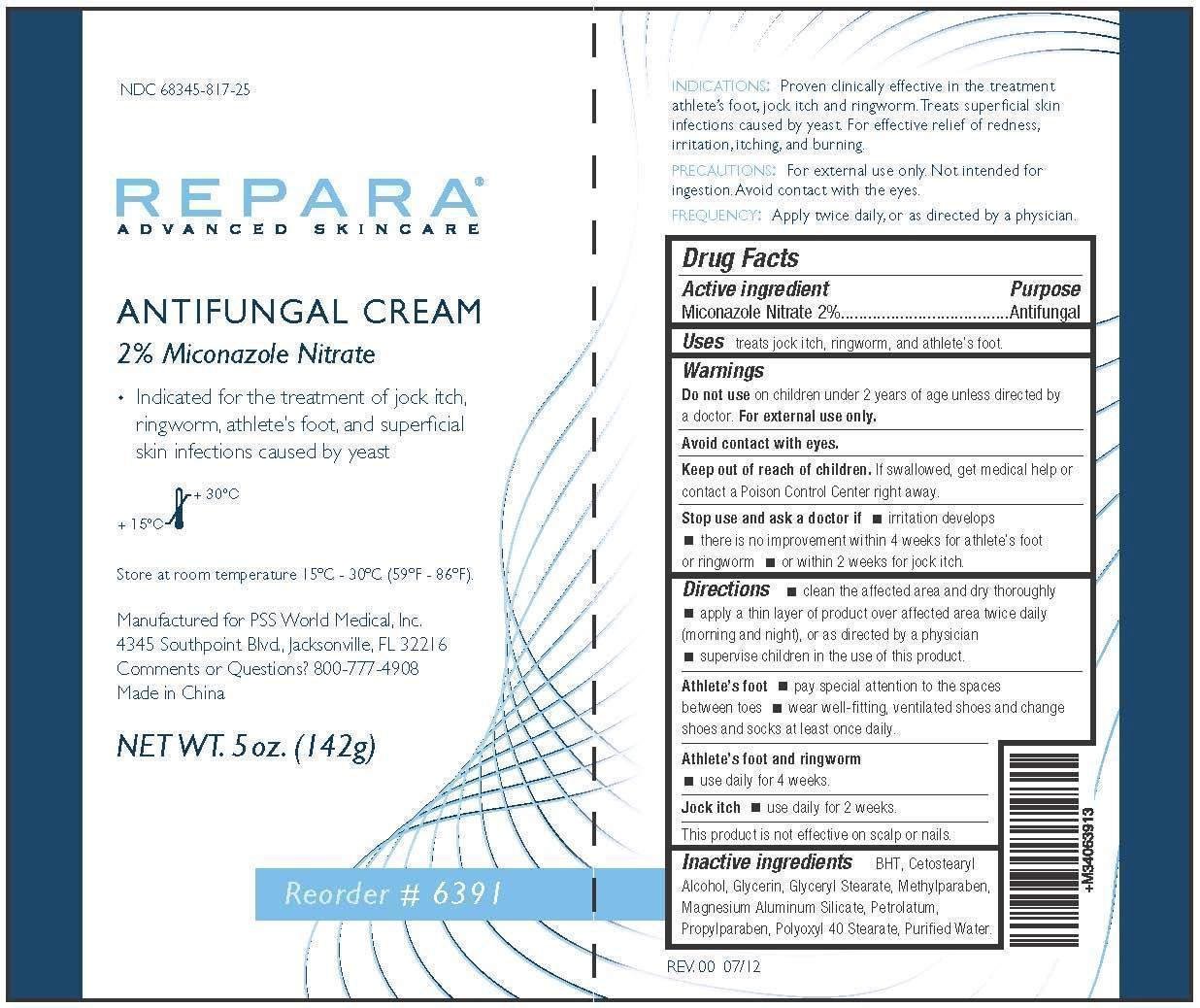 DRUG LABEL: Antifungal
NDC: 68345-817 | Form: CREAM
Manufacturer: PSS World Medical, Inc.
Category: otc | Type: HUMAN OTC DRUG LABEL
Date: 20120927

ACTIVE INGREDIENTS: MICONAZOLE NITRATE 20 mg/1 g
INACTIVE INGREDIENTS: BUTYLATED HYDROXYTOLUENE; CETOSTEARYL ALCOHOL; GLYCERIN; GLYCERYL MONOSTEARATE; METHYLPARABEN; MAGNESIUM ALUMINUM SILICATE; PETROLATUM; PROPYLPARABEN; POLYOXYL 40 STEARATE; WATER

Antifungal Cream

Active Ingredient

Miconazole Nitrate 2%

Purpose

Antifungal

Uses

Treats jock itch, ringworm, and athlete's foot.

INDICATIONS: Proven clinically effective in the treatment athlete's foot, jock itch and ringworm. Treats superficial skin infections caused by yeast. For effective relief of redness, irritation, itching, and burning.

Warnings

For external use only.

PRECAUTIONS: For external use only. Not intended for ingestion. Avoid contact with eyes.

Do not use on children under 2 years of age unless directed by a doctor.

Stop use and ask a doctor if

- irritation develops
- there is no improvement within 4 weeks for athlete's foot or ringworm
- or within 2 weeks for jock itch

Keep out of reach of children. If swallowed, get medical help or contact a Poison Control Center right away.

Directions

- clean the affected area and dry thoroughly
- apply a thin layer of product over affected area twice daily (morning and night), or as directed by a physician
- supervise children in the use of this product

Athlete's Foot

- pay special attention to the spaces between toes
- wear well-fitting, ventilated shoes and change shoes and socks at least once daily

Athlete's Foot and Ringworm

- use daily for 4 weeks

Jock Itch

- use daily for 2 weeks

This product is not effective on scalp or nails.

Inactive Ingredients

BHT, Cetostearyl Alcohol, Glycerin, Glyceryl Stearate, Methylparaben, Magnesium Aluminum Silicate, Petrolatum, Propylparaben, Polyoxyl 40 Stearate, Purified Water.

Questions

Manufactured for PSS World Medical, Inc.

4345 Southpoint Blvd., Jacksonville, FL 32216

Comments or Questions? 800-777-4908

Made in China

Storage

Store at room temperature 15-30C (59-86F).

Package Label

NDC 68345-817-25

6391 Each

6391 Box